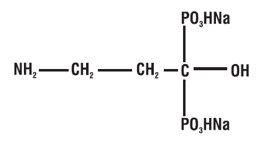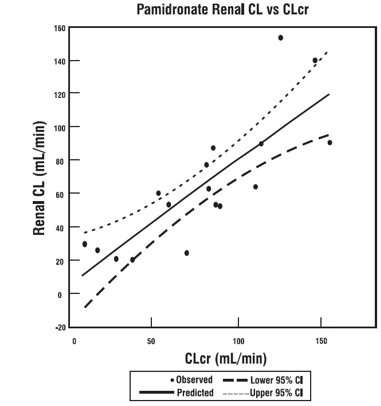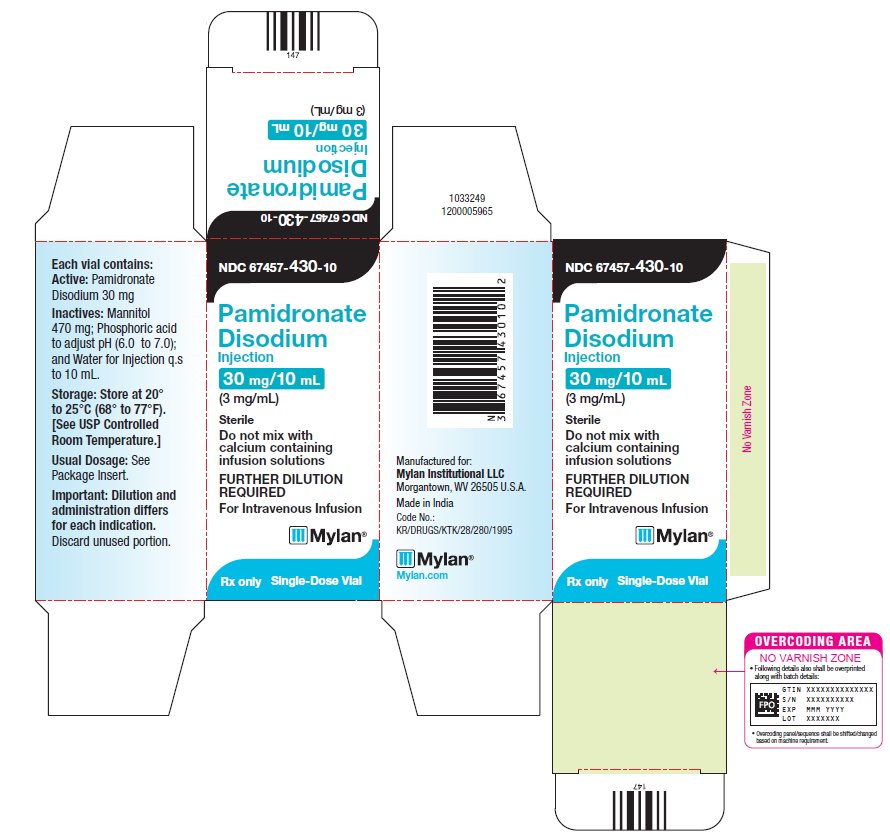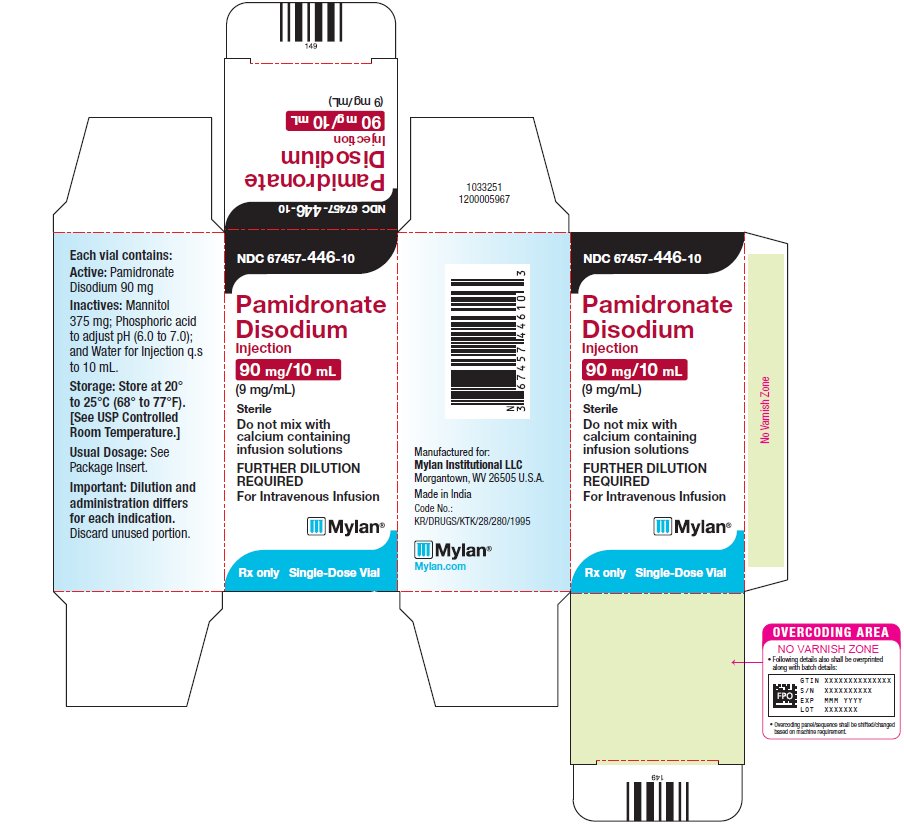 DRUG LABEL: Pamidronate Disodium
NDC: 67457-430 | Form: INJECTION
Manufacturer: Mylan Institutional LLC
Category: prescription | Type: HUMAN PRESCRIPTION DRUG LABEL
Date: 20251215

ACTIVE INGREDIENTS: PAMIDRONATE DISODIUM 3 mg/1 mL
INACTIVE INGREDIENTS: MANNITOL; PHOSPHORIC ACID; WATER

HIGHLIGHTS OF PRESCRIBING INFORMATION

These highlights do not include all the information needed to use PAMIDRONATE DISODIUM INJECTION safely and effectively. See full prescribing information for PAMIDRONATE DISODIUM INJECTION.
PAMIDRONATE DISODIUM injection, for intravenous use
Initial U.S. Approval: 1991

RECENT MAJOR CHANGES

Warnings and Precautions (5.2) 05/2025

1 INDICATIONS AND USAGE

Pamidronate disodium is a bisphosphonate indicated for the treatment of:

- moderate or severe hypercalcemia associated with malignancy, with or without bone metastases (1.1)
- patients with moderate to severe Paget’s disease of bone (1.2)
- osteolytic bone metastases of breast cancer or osteolytic lesions of multiple myeloma, in conjunction with standard antineoplastic therapy (1.3)

Limitations of use

Safety and efficacy of pamidronate disodium in the treatment of hypercalcemia associated with hyperparathyroidism or with other non-tumor-related conditions have not been established. (1.4)

2 DOSAGE AND ADMINISTRATION

- Hypercalcemia of malignancy: 60 mg to 90 mg pamidronate disodium as a single dose infused over 2 hours to 24 hours for moderate hypercalcemia, or 90 mg as a single dose infused over 2 hours to 24 hours for severe hypercalcemia. If warranted, retreat after a minimum of 7 days. (2.1)
- Paget’s disease of bone: 30 mg pamidronate disodium daily as a 4-hour infusion on 3 consecutive days. (2.2)
- Osteolytic Bone Metastases of Breast Cancer: 90 mg pamidronate disodium as a 2-hour infusion every 3 to 4 weeks. Retreat after recovery of renal function. (2.3)
- Osteolytic Bone Lesions of Multiple Myeloma: 90 mg pamidronate disodium as a 4-hour infusion once every four weeks. Retreat after recovery of renal function. (2.3)
- Administer through a separate infusion line. Do not allow pamidronate disodium infusion to come in contact with any calcium or divalent cation-containing solutions. (2.6)

3 DOSAGE FORMS AND STRENGTHS

- Injection: 30 mg/10 mL (3 mg/mL) and 90 mg/10 mL (9 mg/mL) solution in single-dose vials (3)

4 CONTRAINDICATIONS

Hypersensitivity to pamidronate, other bisphosphonates, or mannitol (4)

5 WARNINGS AND PRECAUTIONS

- Renal failure: Do not exceed single doses of 90 mg pamidronate disodium. Assess renal function before each treatment. In patients with bone metastases with severe renal impairment, use of pamidronate disodium is not recommended. (5.1)
- Embryo-Fetal Toxicity: Can cause fetal harm. Advise females of reproductive potential of the potential risk to a fetus and to use effective contraception. (5.2, 8.1, 8.3)
- Electrolyte disorders (e.g., hypophosphatemia, hypokalemia, hypomagnesemia, hypocalcemia): Monitor phosphorus, potassium, magnesium, calcium and vitamin D and adequately supplement as appropriate. (5.3)
- Osteonecrosis of the jaw: Perform preventive dental procedures prior to initiating pamidronate disodium. Avoid invasive procedures if possible in patients receiving pamidronate disodium. (5.4)
- Atypical fractures of the femur can occur after minimal or no trauma. Evaluate patients with thigh or groin pain for possible fracture. (5.5)

6 ADVERSE REACTIONS

Most common adverse reactions per indication:

- Hypercalcemia of malignancy (≥ 15%): Fever, nausea, infusion site reactions, hypocalcemia, hypophosphatemia (6.1)
- Paget’s disease (≥ 10%): Temperature increase, hypertension, arthrosis, bone pain, headache (6.1)
- Osteolytic bone metastases of breast cancer or osteolytic lesions of multiple myeloma (≥ 30%): Skeletal pain, nausea, anemia, fever, fatigue, vomiting, dyspnea (6.1)

To report SUSPECTED ADVERSE REACTIONS, contact Mylan at 1-877-446-3679 (1-877-4-INFO-RX) or FDA at 1-800-FDA-1088 or www.fda.gov/medwatch.

7 DRUG INTERACTIONS

- Nephrotoxic drugs: Use with caution. (7.1)
- Thalidomide: Increased risk of renal dysfunction in patients with multiple myeloma. (7.2)

8 USE IN SPECIFIC POPULATIONS

- Lactation: Advise not to breastfeed. (8.2)
- Infertility: May impair fertility. (8.3)

FULL PRESCRIBING INFORMATION

1 INDICATIONS AND USAGE

1.1 Hypercalcemia of Malignancy

Pamidronate disodium is indicated for the treatment of moderate or severe hypercalcemia associated with malignancy, with or without bone metastases.

1.2 Paget’s Disease

Pamidronate disodium is indicated for the treatment of patients with moderate to severe Paget’s disease of bone.

1.3 Osteolytic Bone Metastases of Breast Cancer and Osteolytic Lesions of Multiple Myeloma

Pamidronate disodium is indicated in conjunction with standard antineoplastic therapy, for the treatment of osteolytic bone metastases of breast cancer and osteolytic lesions of multiple myeloma [see Clinical Studies (14.3)].

1.4 Limitations of Use

The safety and efficacy of pamidronate disodium in the treatment of hypercalcemia associated with hyperparathyroidism or with other non-tumor-related conditions has not been established.

2 DOSAGE AND ADMINISTRATION

2.1 Hypercalcemia of Malignancy

Vigorous saline hydration, should be initiated promptly along with pamidronate therapy and if possible the urine output should be about 2 L/day throughout treatment [see Warnings and Precautions (5.2)].

Patients who receive pamidronate disodium should have serum creatinine assessed prior to each treatment [see Warnings and Precautions (5.1)]. Treatment should be withheld for renal deterioration.

Moderate Hypercalcemia

The recommended dose of pamidronate disodium in moderate hypercalcemia (corrected serum calcium* of approximately 12 mg/dL to 13.5 mg/dL) is 60 mg to 90 mg given as a single-dose, intravenous infusion over 2 hours to 24 hours. Longer infusions (i.e., greater than 2 hours) may reduce the risk for renal toxicity, particularly in patients with preexisting renal impairment.

Severe Hypercalcemia

The recommended dose of pamidronate disodium in severe hypercalcemia (corrected serum calcium* > 13.5 mg/dL) is 90 mg given as a single-dose, intravenous infusion over 2 to 24 hours. Longer infusions (i.e., greater than 2 hours) may reduce the risk for renal toxicity, particularly in patients with preexisting renal insufficiency/impairment.

*Albumin-corrected serum calcium = serum calcium, mg/dL + 0.8 (4.0-serum albumin, g/dL).

Retreatment

Retreatment with pamidronate disodium in patients who show complete or partial response initially may be carried out if serum calcium does not return to normal or remain normal after initial treatment. A minimum of 7 days between treatments is recommended to allow for full response to the initial dose. The dose and manner of retreatment is identical to that of the initial therapy.

2.2 Paget’s Disease

The recommended dose of pamidronate disodium in patients with moderate to severe Paget’s disease of bone is 30 mg daily, administered as a 4-hour infusion on 3 consecutive days for a total dose of 90 mg. When clinically indicated, patients should be retreated at the dose of initial therapy.

2.3 Osteolytic Bone Metastases of Breast Cancer and Osteolytic Lesions of Multiple Myeloma

Osteolytic Bone Metastases of Breast Cancer

The recommended dose of pamidronate disodium in patients with osteolytic bone metastases is 90 mg administered over a 2-hour infusion given every 3 to 4 weeks.

In a clinical study, renal deterioration was defined as follows:

- With normal baseline creatinine, an increase of 0.5 mg/dL.
- With abnormal baseline creatinine, an increase of 1 mg/dL.

In this clinical study, pamidronate disodium treatment was resumed only when the creatinine

returned to within 10% of the baseline value.

The optimal duration of therapy is not known; however, in two breast cancer studies, final analyses performed after 24 months of therapy demonstrated overall benefits [see Clinical Studies (14.3)].

Osteolytic Bone Lesions of Multiple Myeloma

The recommended dose of pamidronate disodium in patients with osteolytic bone lesions of multiple myeloma is 90 mg administered as a 4-hour infusion administered every four weeks.

Patients with marked Bence-Jones proteinuria and dehydration should receive adequate hydration prior to pamidronate disodium infusion.

Limited information is available on the use of pamidronate disodium in multiple myeloma patients with a serum creatinine greater than or equal to 3 mg/dL.

Patients who receive pamidronate disodium should have serum creatinine assessed prior to each treatment. Treatment should be withheld for renal deterioration.

In a clinical study, renal deterioration was defined as follows:

- With normal baseline creatinine, an increase of 0.5 mg/dL.
- With abnormal baseline creatinine, an increase of 1 mg/dL.

In this clinical study, pamidronate disodium treatment was resumed only when the creatinine returned to within 10% of the baseline value.

The optimal duration of therapy is not known. However, in a study of patients with myeloma, final analysis after 21 months demonstrated overall benefits [see Clinical Studies (14.3)].

2.5 Dilution for Administration

Hypercalcemia of Malignancy

The daily dose must be administered as an intravenous infusion over at least 2 hours and up to 24 hours for the 60 mg and 90 mg doses. The recommended dose should be diluted in 1000 mL of sterile 0.45% or 0.9% sodium chloride injection or 5% dextrose injection. This infusion solution is stable for up to 24 hours at room temperature.

Paget’s Disease

The recommended daily dose of 30 mg should be diluted in 500 mL of sterile 0.45% or 0.9% sodium chloride injection, or 5% dextrose injection and administered over a 4-hour period daily for 3 consecutive days.

Osteolytic Bone Metastases of Breast Cancer

The recommended dose of 90 mg should be diluted in 250 mL of sterile 0.45% or 0.9% sodium chloride injection or 5% dextrose injection and administered over a 2-hour period once every 3 to 4 weeks.

Osteolytic Bone Lesions of Multiple Myeloma

The recommended dose of 90 mg should be diluted in 500 mL of sterile 0.45% or 0.9% sodium chloride injection, or 5% dextrose injection, and administered over a 4-hour period every four weeks.

2.6 Incompatibilities, Inspection before Use

Pamidronate disodium must not be mixed with calcium-containing infusion solutions such as Ringer’s solution. Administer as a single intravenous solution and infuse using an intravenous line reserved for pamidronate alone.

Parenteral drug products should be inspected visually for particulate matter and discoloration prior to administration, whenever solution and container permit.

3 DOSAGE FORMS AND STRENGTHS

Injection: 30 mg/10 mL (3 mg/mL) and 90 mg/10 mL (9 mg/mL) solution in single-dose vials

4 CONTRAINDICATIONS

Pamidronate disodium is contraindicated in patients with hypersensitivity to pamidronate disodium, other bisphosphonates, or mannitol. Reactions to pamidronate disodium injection and to mannitol have included anaphylaxis.

5 WARNINGS AND PRECAUTIONS

5.1 Deterioration in Renal Function, Use in Patients with Renal Impairment

Bisphosphonates, such as pamidronate disodium, have been associated with renal toxicity, including focal segmental glomerulosclerosis. This toxicity has been manifested as nephritic syndrome, deterioration of renal function, and renal failure. Renal failure has been reported in patients after a single dose of pamidronate disodium. Some patients had gradual improvement in renal status after pamidronate disodium was discontinued.

Do not administer single doses of pamidronate disodium in excess of 90 mg due to the risk of clinically significant deterioration in renal function, [see Dosage and Administration (2.5)].

Assess serum creatinine prior to each treatment. Withhold treatment until renal function returns to baseline in patients who show evidence of deterioration in renal function. Do not administer pamidronate in patients with severe renal impairment for the treatment of bone metastases [see Dosage and Administration (2.1, 2.2, 2.3)].

5.2 Embryo-Fetal Toxicity

Based on findings in animals and its mechanism of action, pamidronate disodium can cause fetal harm when administered to a pregnant woman [see Clinical Pharmacology (12.1)]. In reproductive studies, administration of pamidronate to pregnant rats and rabbits at doses equivalent to 0.6 to 8.3 times the highest human recommended dose resulted in maternal toxicity and embryo-fetal effects.

Bisphosphonates, such as pamidronate disodium, are incorporated into the bone matrix, from where they are gradually released over periods of weeks to years. There may be a risk of fetal harm (e.g., skeletal and other abnormalities) if a woman becomes pregnant after completing a course of bisphosphonate therapy. Advise pregnant women and females of reproductive potential of the potential risk to a fetus. Advise females of reproductive potential to use effective contraception during and after pamidronate disodium treatment [see Use in Specific Populations (8.1, 8.3)].

5.3 Electrolyte Disorders

Cases of asymptomatic hypophosphatemia (12%), hypokalemia (7%), hypomagnesemia (11%), and hypocalcemia (5% to 17%), were reported in pamidronate disodium-treated patients. Cases of symptomatic hypocalcemia (including tetany) have been reported in association with pamidronate disodium therapy. Monitor serum levels of calcium, phosphate, magnesium, and potassium, following initiation of therapy with pamidronate disodium. If hypocalcemia occurs, short-term calcium therapy may be necessary. In the absence of hypercalcemia, supplement with oral calcium and vitamin D in order to minimize the risk of hypocalcemia.

5.4 Osteonecrosis of the Jaw

Osteonecrosis of the jaw (ONJ) has been reported predominantly in cancer patients treated with intravenous bisphosphonates, including pamidronate disodium. Many of these patients were also receiving chemotherapy and corticosteroids, which may be risk factors for ONJ. Postmarketing experience and the literature suggest a greater frequency of ONJ with certain tumor type (advanced breast cancer, multiple myeloma), and dental status (dental extraction, periodontal disease, local trauma including poorly fitting dentures). Local infection including osteomyelitis has been reported with ONJ.

Patients receiving pamidronate should maintain good oral hygiene and have a dental examination with preventive dentistry prior to initiation of treatment.

While on treatment, avoid invasive dental procedures if possible. For patients who develop ONJ while on bisphosphonate therapy, dental surgery may exacerbate the condition. For patients requiring dental procedures, there are no data available to suggest whether discontinuation of bisphosphonate treatment reduces the risk of ONJ. Clinical judgment of the treating physician should guide the management plan of each patient based on individual benefit/risk assessment [see Adverse Reactions (6.2)].

5.5 Atypical Fractures of the Femur

Atypical subtrochanteric and diaphyseal femoral fractures have been reported in patients receiving bisphosphonate therapy, including pamidronate disodium. These fractures can occur anywhere in the femoral shaft from just below the lesser trochanter to just above the supracondylar flare and are transverse or short oblique in orientation without evidence of comminution. These fractures may occur after minimal or no trauma. Patients may experience thigh or groin pain weeks to months before presenting with a completed femoral fracture. Fractures are often bilateral; therefore, the contralateral femur should be examined in bisphosphonate-treated patients who have sustained a femoral shaft fracture. Poor healing of these fractures also has been reported. A number of case reports noted that patients were receiving treatment also with glucocorticoids (such as prednisone or dexamethasone) at the time of fracture. Causality with bisphosphonate therapy has not been established.

Any patient with a history of bisphosphonate exposure who presents with thigh or groin pain in the absence of trauma should be evaluated for an atypical fracture. Consider discontinuation of pamidronate disodium therapy in patients suspected to have an atypical femur fracture pending evaluation of the patient, based on an individual benefit risk assessment. It is unknown whether the risk of atypical femur fracture continues after stopping therapy.

6 ADVERSE REACTIONS

The following adverse reactions are described, or described in greater detail, in other sections:

- Deterioration in renal function [see Warnings and Precautions (5.1)]
- Electrolyte disorders [see Warnings and Precautions (5.3)]
- Osteonecrosis of the jaw [see Warnings and Precautions (5.4)]
- Atypical fractures of the femur [see Warnings and Precautions (5.5)]

6.1 Clinical Trials Experience

Because clinical trials are conducted under widely varying conditions, adverse reaction rates observed in the clinical trials of a drug cannot be directly compared to rates in the clinical trials of another drug and may not reflect the rates observed in practice.

Hypercalcemia of Malignancy

Transient elevation of temperature by at least 1°C was noted 24 to 48 hours after administration of pamidronate disodium in 34% of patients in clinical trials. Local soft-tissue reactions (redness, swelling or induration and pain on palpation) at the site of catheter insertion were observed, most commonly in patients treated with 90 mg of pamidronate disodium. Symptomatic treatment resulted in resolution in all patients.

Cases of uveitis, iritis, scleritis, and episcleritis have been reported, including one case of scleritis and one case of uveitis upon separate rechallenges.

Five of 231 patients (2%) who received pamidronate disodium while enrolled on controlled

clinical trials for management of hypercalcemia were reported to have seizures, including two patients with pre-existing seizure disorders. One patient on the control (saline arm) also had a seizure. At least 15% of patients treated with pamidronate disodium for hypercalcemia of malignancy experienced the following adverse reactions during a clinical trial:

General: Fluid overload, generalized pain

Cardiovascular: Hypertension

Gastrointestinal: Abdominal pain, anorexia, constipation, nausea, vomiting

Genitourinary: Urinary tract infection

Musculoskeletal: Bone pain

Laboratory abnormality: Anemia, hypokalemia, hypomagnesemia, hypophosphatemia

Table 1 lists the adverse reactions reported during comparative, controlled trials.

Table 1: Adverse Reactions Reported in Three U.S. Controlled Clinical Trials
 | Percent of Patients
 | Pamidronate Disodium |  |  | Etidronate Disodium | Saline
 | 60 mg over 4 hr | 60 mg over 24 hr | 90 mg over 24 hr | 7.5 mg/kg x 3 days
 | n = 23 | n = 73 | n = 17 | n = 35 | n = 23
General
Edema | 0 | 1 | 0 | 0 | 0
Fatigue | 0 | 0 | 12 | 0 | 0
Fever | 26 | 19 | 18 | 9 | 0
Infusion-site reaction | 0 | 4 | 18 | 0 | 0
Moniliasis | 0 | 0 | 6 | 0 | 0
Gastrointestinal
Abdominal pain | 0 | 1 | 0 | 0 | 0
Anorexia | 4 | 1 | 12 | 0 | 0
Constipation | 4 | 0 | 6 | 3 | 0
Diarrhea | 0 | 1 | 0 | 0 | 0
Dyspepsia | 4 | 0 | 0 | 0 | 0
Gastrointestinal hemorrhage | 0 | 0 | 6 | 0 | 0
Nausea | 4 | 0 | 18 | 6 | 0
Stomatitis | 0 | 1 | 0 | 3 | 0
Vomiting | 4 | 0 | 0 | 0 | 0
Respiratory
Rales | 0 | 0 | 6 | 0 | 0
Rhinitis | 0 | 0 | 6 | 0 | 0
Upper respiratory infection | 0 | 3 | 0 | 0 | 0
CNS
Insomnia | 0 | 1 | 0 | 0 | 0
Psychosis | 4 | 0 | 0 | 0 | 0
Somnolence | 0 | 1 | 6 | 0 | 0
Cardiovascular
Atrial fibrillation | 0 | 0 | 6 | 0 | 4
Atrial flutter | 0 | 1 | 0 | 0 | 0
Cardiac failure | 0 | 1 | 0 | 0 | 0
Hypertension | 0 | 0 | 6 | 0 | 4
Syncope | 0 | 0 | 6 | 0 | 0
Tachycardia | 0 | 0 | 6 | 0 | 4
Endocrine
Hypothyroidism | 0 | 0 | 6 | 0 | 0
Hemic and Lymphatic
Anemia | 0 | 0 | 6 | 0 | 0
Leukopenia | 4 | 0 | 0 | 0 | 0
Neutropenia | 0 | 1 | 0 | 0 | 0
Thrombocytopenia | 0 | 1 | 0 | 0 | 0
Musculoskeletal
Myalgia | 0 | 1 | 0 | 0 | 0
Urogenital
Uremia | 4 | 0 | 0 | 0 | 0
Laboratory Abnormalities
Hypocalcemia | 0 | 1 | 12 | 0 | 0
Hypokalemia | 4 | 4 | 18 | 0 | 0
Hypomagnesemia | 4 | 10 | 12 | 3 | 4
Hypophosphatemia | 0 | 9 | 18 | 3 | 0

Paget’s Disease

Adverse reactions that occurred in at least 5% of patients with Paget’s disease treated with

90 mg of pamidronate disodium in two clinical trials included fever, nausea, back pain, and bone pain. Dizziness, headaches, parathesias, and increased sweating were also reported and occurred more frequently than reported in patients treated with pamidronate for hypercalcemia of malignancy.

At least 10% of all pamidronate disodium-treated patients with Paget’s disease also experienced the following adverse reactions during clinical trials:

Cardiovascular: Hypertension

Musculoskeletal: Arthrosis, bone pain

Nervous system: Headache

Osteolytic Bone Metastases of Breast Cancer and Osteolytic Lesions of Multiple Myeloma

The most commonly reported (> 15%) adverse reactions occurred with similar frequencies in the pamidronate disodium and in the placebo group (see Table 2).

Table 2: Commonly Reported Adverse Reactions in Three U.S. Controlled Clinical Trials
 | Pamidronate Disodium 90 mg over 4 hours | Placebo | Pamidronate Disodium 90 mg over 2 hours | Placebo | All; Pamidronate Disodium 90 mg | Placebo
 | N = 205 % | N = 187 % | N = 367 % | N = 386 % | N = 572 % | N = 573 %
General
Asthenia | 16 | 17 | 26 | 19 | 22 | 19
Fatigue | 32 | 28 | 40 | 29 | 37 | 29
Fever | 39 | 38 | 38 | 32 | 39 | 34
Metastases | 1 | 3 | 31 | 24 | 21 | 18
Pain | 13 | 12 | 15 | 18 | 14 | 16
Digestive System
Anorexia | 17 | 17 | 31 | 25 | 26 | 22
Diarrhea | 27 | 27 | 29 | 31 | 29 | 30
Dyspepsia | 18 | 13 | 18 | 15 | 23 | 18
Nausea | 36 | 37 | 64 | 59 | 54 | 52
Pain Abdominal | 20 | 16 | 24 | 18 | 23 | 18
Vomiting | 17 | 20 | 46 | 39 | 36 | 33
Hemic and Lymphatic
Anemia | 48 | 42 | 40 | 37 | 43 | 38
Granulocytopenia | 21 | 16 | 19 | 21 | 20 | 19
Musculoskeletal System
Arthralgias | 11 | 7 | 15 | 13 | 14 | 11
Myalgia | 25 | 15 | 26 | 23 | 26 | 20
Skeletal Pain | 61 | 72 | 70 | 75 | 67 | 74
CNS
Anxiety | 8 | 9 | 18 | 17 | 14 | 14
Headache | 24 | 20 | 27 | 24 | 26 | 22
Insomnia | 17 | 17 | 25 | 19 | 22 | 19
Respiratory System
Coughing | 26 | 23 | 25 | 20 | 26 | 21
Dyspnea | 22 | 21 | 35 | 24 | 30 | 23
Pleural Effusion | 3 | 4 | 15 | 9 | 11 | 8
Sinusitis | 15 | 17 | 16 | 10 | 16 | 12
Upper Respiratory; Tract Infection | 32 | 28 | 20 | 20 | 24 | 23
Urogenital System
Urinary Tract Infection | 16 | 9 | 20 | 18 | 19 | 16

In the breast cancer trials, four pamidronate disodium-related adverse reactions, interstitial pneumonitis, malaise and dyspnea, symptomatic hypocalcemia, and severe bone pain, resulted in discontinuation of therapy.

6.2 Postmarketing Experience

The following adverse reactions have been identified during postapproval pamidronate sodium use. Because these reactions are reported voluntarily from a population of uncertain size, it is not possible to reliably estimate their frequency or establish a causal relationship to drug exposure.

General: reactivation of Herpes simplex and Herpes zoster, influenza-like symptoms

CNS: confusion and visual hallucinations, sometimes in the presence of electrolyte imbalance

Skin: rash, pruritus

Special senses: conjunctivitis, orbital inflammation

Renal and urinary disorders: focal segmental glomerulosclerosis including the collapsing variant, nephrotic syndrome; renal tubular disorders (RTD); tubulointerstitial nephritis, and glomerulonephropathies.

Laboratory abnormalities: hyperkalemia, hypernatremia, hematuria. Cases of allergic manifestations have been reported, including hypotension, dyspnea, or angioedema, and anaphylactic shock. Pamidronate disodium is contraindicated in patients with clinically significant hypersensitivity to pamidronate disodium or other bisphosphonates [see Contraindications (4)].

Respiratory, thoracic and mediastinal disorders: adult respiratory distress syndrome (ARDS), interstitial lung disease (ILD).

Musculoskeletal and connective tissue disorders: severe, occasionally incapacitating bone, joint, and/or muscle pain.

7 DRUG INTERACTIONS

7.1 Nephrotoxic Drugs

Caution is indicated when pamidronate disodium is used with other potentially nephrotoxic drugs.

7.2 Thalidomide

In multiple myeloma patients, the risk of renal deterioration may be increased when pamidronate disodium is used in combination with thalidomide.

7.3 Loop Diuretics

Concomitant administration of a loop diuretic had no effect on the calcium-lowering action of pamidronate disodium.

8 USE IN SPECIFIC POPULATIONS

8.1 Pregnancy

Risk Summary

Based on findings from animal studies and its mechanism of action [see Clinical Pharmacology (12.1)], pamidronate disodium can cause fetal harm when administered to a pregnant woman. Available data from case reports with pamidronate disodium use in pregnant women are insufficient to inform a drug-associated risk. Administration of pamidronate to pregnant rats and rabbits resulted in maternal toxicity and embryo-fetal effects (see Data).

Bisphosphonates, such as pamidronate disodium, are incorporated into the bone matrix, from where they are gradually released over periods of weeks to years. There may be a risk of fetal harm (e.g., skeletal and other abnormalities) if a woman becomes pregnant after completing a course of bisphosphonate therapy. Advise pregnant women and females of reproductive potential of the potential risk to a fetus.

In the U.S. general population, the estimated background risk of major birth defects and

miscarriage in clinically recognized pregnancies is 2% to 4% and 15% to 20%, respectively.

Data

Animal Data

In animal reproduction studies, intravenous administration of pamidronate to pregnant rats and rabbits during the period of organogenesis resulted in maternal toxicity and embryo-fetal effects at doses of 0.6 to 8.3 times the highest recommended human dose for a single intravenous infusion.

8.2 Lactation

Risk Summary

There are limited data on the presence of pamidronate or its metabolites in human milk, its effects on a breastfed child, or its effects on milk production.

Pamidronate disodium binds to bone long term and may be released over periods of weeks to years. Because of the potential for serious adverse reactions in a breastfed child, advise lactating women not to breastfeed during and after pamidronate disodium treatment.

8.3 Females and Males of Reproductive Potential

Pamidronate disodium can cause fetal harm when administered to a pregnant woman [see Use in Specific Populations (8.1)].

Pregnancy Testing

Verify pregnancy status of females of reproductive potential prior to initiation of pamidronate disodium.

Contraception

Females

Pamidronate disodium binds to bone long term and may be released over periods of weeks to years. Advise females of reproductive potential to use effective contraception during and after pamidronate disodium treatment.

Infertility

Based on animal studies, pamidronate disodium may impair fertility in males and females of reproductive potential [see Nonclinical Toxicology (13.1)].

8.4 Pediatric Use

Safety and effectiveness of pamidronate disodium in pediatric patients have not been established.

8.5 Geriatric Use

Of the total number of subjects in clinical studies of pamidronate disodium, approximately 20% were 65 and over, while approximately 15% were 75 and over. No overall differences in safety or effectiveness were observed between these subjects and younger subjects, and other reported clinical experience has not identified differences in responses between the elderly and younger patients, but greater sensitivity of some older individuals cannot be ruled out. In general, dose selection for an elderly patient should be cautious, usually starting at the low end of the dosing range, reflecting the greater frequency of decreased hepatic, renal, or cardiac function, and of concomitant disease or other drug therapy.

8.6 Patients with Renal Impairment

The renal clearance of pamidronate was reduced in patients with reduced creatinine clearance. Because pamidronate disodium is administered on a monthly basis, drug accumulation is not expected. No changes in pamidronate disodium dosing regimen are recommended for patients with mild to moderate renal impairment (creatinine clearance > 30 mL/min). Limited pharmacokinetic data exist in patients with creatinine clearance < 30 mL/min [see Warnings and Precautions (5.1) and Clinical Pharmacology (12.3)].

8.7 Patients with Hepatic Impairment

Patients with moderate hepatic impairment exhibited higher mean pamidronate AUC and Cmax. Because pamidronate disodium is administered on a monthly basis, drug accumulation is not expected. No changes in pamidronate disodium dosing regimen are recommended for patients with mild to moderate hepatic impairment. Pamidronate disodium has not been studied in patients with severe hepatic impairment [see Clinical Pharmacology (12.3)].

10 OVERDOSAGE

Cases of drug overdose have been reported in hypercalcemia patients treated with total doses of 225 mg to 300 mg pamidronate disodium given over 2.5 to 4 days. All patients survived, but all developed hypocalcemia that required intravenous and/or oral administration of calcium. If overdosage occurs, treat symptomatic hypocalcemia patients with short-term intravenous calcium.

Single doses of pamidronate disodium should not exceed 90 mg, and the duration of the intravenous infusion should be no less than 2 hours [see Dosage and Administration (2.5) and Warnings and Precautions (5.1)].

In addition, one obese woman (95 kg) who was treated with 285 mg of pamidronate disodium/day for 3 days experienced high fever (39.5°C), hypotension (from 170/90 mmHg to 90/60 mmHg), and transient taste perversion, occurring about 6 hours after the first infusion. Fever and hypotension reversed with steroid therapy.

11 DESCRIPTION

Pamidronate Disodium Injection is a bisphosphonate available in 30 mg and 90 mg vials for intravenous administration. Each mL of the 30 mg/10 mL vial contains 3 mg pamidronate disodium, 47 mg mannitol; water for injection, q.s.; and phosphoric acid to adjust pH 6.0 to 7.0. Each mL of the 90 mg/10 mL vial contains, 9 mg pamidronate disodium, 37.5 mg mannitol; water for injection, q.s.; and phosphoric acid to adjust pH 6.0 to 7.0.

The pH of a 1% solution of pamidronate disodium in distilled water is approximately 8.3.

Pamidronate disodium, a member of the group of chemical compounds known as bisphosphonates, is an analog of pyrophosphate. Pamidronate disodium is designated chemically as phosphonic acid (3-amino-1-hydroxypropylidene) bis-, disodium salt, and its structural formula is:

Pamidronate disodium is a white powder. It is soluble in water and in 2N sodium hydroxide, sparingly soluble in 0.1N hydrochloric acid and in 0.1N acetic acid, and practically insoluble in organic solvents. Its molecular formula is C3H9NO7P2Na2 and its molecular weight is 279.1 (calculated as the anhydrous form).

12 CLINICAL PHARMACOLOGY

12.1 Mechanism of Action

The principal pharmacologic action of pamidronate disodium is inhibition of bone resorption. Although the mechanism of antiresorptive action is not completely understood, several factors are thought to contribute to this action. Pamidronate disodium adsorbs to calcium phosphate (hydroxyapatite) crystals in bone and may block dissolution of this mineral component of bone. In vitro, pamidronate disodium inhibited osteoclast activity. In animal studies, pamidronate disodium inhibited bone resorption, but did not inhibit bone formation and mineralization. In animal tumor models, pamidronate disodium inhibited the increased osteoclast activity induced by tumors.

12.2 Pharmacodynamics

Serum phosphate levels have been noted to decrease after administration of pamidronate disodium, presumably because of decreased release of phosphate from bone and increased renal excretion as parathyroid hormone levels, which are usually suppressed in hypercalcemia associated with malignancy, return toward normal. Phosphate therapy was administered in 30% of the patients in response to a decrease in serum phosphate levels. Phosphate levels usually returned toward normal within 7 to 10 days.

Urinary calcium/creatinine and urinary hydroxyproline/creatinine ratios decrease and usually return to within or below normal after treatment with pamidronate disodium. These changes occur within the first week after treatment, as do decreases in serum calcium levels, and are consistent with an antiresorptive pharmacologic action.

12.3 Pharmacokinetics

Table 3 shows maximum concentration, percent of dose excreted in urine, total clearance, and renal clearance of pamidronate after an intravenous infusion of 30, 60, or 90 mg of pamidronate disodium over 4 hours and 90 mg of pamidronate disodium over 24 hours in cancer patients (n = 24) who had minimal or no bony involvement.

Table 3: Mean (Standard Deviation, CV%) Pamidronate Pharmacokinetic Parameters in Cancer Patients (n = 6 for each group)
Dose (infusion rate) | Maximum Concentration (mcg/mL) | Percent of dose excreted in urine | Total Clearance (mL/min) | Renal Clearance (mL/min)
30 mg (4 hrs) | 0.73 (0.14, 19.1%) | 43.9 (14.0, 31.9%) | 136 (44, 32.4%) | 58 (27, 46.5%)
60 mg (4 hrs) | 1.44 (0.57, 39.6%) | 47.4 (47.4, 54.4%) | 88 (56, 63.6%) | 42 (28, 66.7%)
90 mg (4 hrs) | 2.61 (0.74, 28.3%) | 45.3 (25.8, 56.9%) | 103 (37, 35.9%) | 44 (16, 36.4%)
90 mg (24 hrs) | 1.38 (1.97, 142.7%) | 47.5 (10.2, 21.5%) | 101 (58, 57.4%) | 52 (42, 80.8%)

Distribution

The body retention of pamidronate was 54 ± 16% (mean ± standard deviation) of the dose over 120 hours.

Metabolism

Pamidronate is not metabolized.

Elimination

The elimination half-life is 28 ± 7 hours (mean ± standard deviation). Total and renal clearances of pamidronate were 107 ± 50 mL/min and 49 ± 28 mL/min, respectively. The rate of elimination from bone has not been determined.

After administration of 30, 60, and 90 mg of pamidronate disodium over 4 hours, and 90 mg of pamidronate disodium over 24 hours, 46 ± 16% (mean ± standard deviation) of the drug was excreted unchanged in the urine within 120 hours. Cumulative urinary excretion was linearly related to dose.

Specific Populations

Renal Impairment

The pharmacokinetics of pamidronate were studied in cancer patients (n = 19) with normal and varying degrees of renal impairment. Each patient received a single 90 mg dose of pamidronate disodium infused over 4 hours. Renal clearance correlated with creatinine clearance (see Figure 1). Because pamidronate disodium is administered on a monthly basis, drug accumulation is not expected.

Figure 1: Pamidronate renal clearance as a function of creatinine clearance in patients with normal and impaired renal function. The lines are the mean prediction line and 95% confidence intervals.

Hepatic Impairment

The pharmacokinetics of pamidronate were studied in male cancer patients at risk for bone metastases with normal hepatic function (n = 6) and mild to moderate hepatic dysfunction (n = 7). Each patient received a single 90 mg dose of pamidronate disodium infused over 4 hours. Although there was a difference in the pharmacokinetics between patients with normal and impaired hepatic function, the difference was not considered clinically relevant. Patients with hepatic impairment exhibited higher mean AUC (53% increase) and Cmax (29% increase), and decreased plasma clearance (33% decrease) values. Because pamidronate disodium is administered on a monthly basis, drug accumulation is not expected.

13 NONCLINICAL TOXICOLOGY

13.1 Carcinogenesis, Mutagenesis, Impairment of Fertility

In a 104-week carcinogenicity study with daily oral administration of pamidronate in rats, there was a positive dose-response relationship for benign adrenal pheochromocytoma. The lowest daily dose associated with adrenal pheochromocytoma resulted in systemic exposures that were similar to the systemic exposure achieved in patients at the intended clinical dose. Adrenal pheochromocytoma also was observed in low numbers in the control animals and is considered a relatively common spontaneous neoplasm in the rat. Pamidronate given daily by oral administration was not carcinogenic in an 80 week study in mice.

Pamidronate was not genotoxic in the Ames bacterial mutagenicity assay, nucleus-anomaly test, sister-chromatid-exchange study, and point-mutation test. Pamidronate was not genotoxic in the in vivo rat micronucleus assay.

In rats, decreased fertility occurred in first-generation offspring of parents who had received 150 mg/kg of pamidronate orally; however, this occurred only when animals were mated with members of the same dose group.

13.2 Animal Toxicology and/or Pharmacology

After intravenous administration of radiolabeled pamidronate in rats, approximately 50% to 60% of the compound was rapidly adsorbed by bone and slowly eliminated from the body by the kidneys. In rats given 10 mg/kg bolus injections of radiolabeled pamidronate disodium, approximately 30% of the compound was found in the liver shortly after administration and was then redistributed to bone or eliminated by the kidneys over 24 to 48 hours. Studies in rats injected with radiolabeled pamidronate disodium showed that the compound was rapidly cleared from the circulation and taken up mainly by bones, liver, spleen, teeth, and tracheal cartilage. Radioactivity was eliminated from most soft tissues within 1 to 4 days; was detectable in liver and spleen for 1 and 3 months, respectively; and remained high in bones, trachea, and teeth for 6 months after dosing. Bone uptake occurred preferentially in areas of high bone turnover. The terminal phase of elimination half-life in bone was estimated to be approximately 300 days.

14 CLINICAL STUDIES

14.1 Hypercalcemia of Malignancy

In one double-blind clinical trial, 52 patients who had hypercalcemia of malignancy received 30 mg, 60 mg, or 90 mg of pamidronate disodium as a single 24-hour intravenous infusion if their corrected serum calcium levels were ≥ 12 mg/dL after 48-hours of saline hydration (See Table 4).

Table 4: Comparison of Calcium Normalization Following a 24-hour Infusion of Pamidronate Disodium
Pamidronate Disodium | 30 mg | 60 mg | 90 mg
Mean Baseline Corrected Serum Calcium (after 48 hours saline hydration) | 13.8 mg/dL | 13.8 mg/dL | 13.3 mg/dL
% Patients with Normalized Serum Calcium (N = 52)
Day 7 | 41% | 61% | 100%
Day 14 | ---- | 33% | 53%

In a second double-blind, controlled clinical trial, 65 cancer patients who had corrected serum calcium levels of ≥ 12 mg/dL after at least 24-hours of saline hydration were randomized to receive either 60 mg of pamidronate disodium as a single 24-hour intravenous infusion or 7.5 mg/kg of etidronate disodium as a 2-hour intravenous infusion daily for 3 days. Results are shown in Table 5.

Table 5: Calcium Levels, Percentage of Patients with Response over Time, and Median Duration of Response
 | Pamidronate Disodium; 60 mg/24-hours (N = 30) | Etidronate Disodium 7.5 mg/kg/2-hours (N = 35) | P-value
Mean Corrected Serum Calcium Level
Baseline | 14.6 mg/dL | 13.8 mg/dL
At Day 7 | 10.4 mg/dL | 11.2 mg/dL
% Patients with Normalized Serum Calcium Level or > 15% from Baseline
At Day 7 | 97% | 65% | P < 0.01
At Day 14 | 43% | 18%
Median Duration of Response
 | 7 days | 5 days

In a third multicenter, randomized, parallel, double-blind trial, 69 patients with cancer, who had a corrected serum calcium level of ≥ 12 mg/dL after 24 hours of saline hydration, received 60 mg of pamidronate disodium as a 4-or 24-hour infusion or a saline control (Table 6).

Table 6: Comparison of Pamidronate Disodium 4-hour, 24-hours Infusion with Saline Control
 | Pamidronate Disodium; 60 mg/4 hours | Pamidronate Disodium; 60 mg/24 hours | Saline Control
Baseline Corrected Serum Calcium | 14.2 mg/dL | 13.7 mg/dL | 13.7 mg/dL
% Patients with Normalized Serum Calcium (N = 69)
At Day 7 | 78% | 61% | 22%
At Day 14 | 39% | 26% | ---
Median Duration of Complete Response
Days | 4 | 6.5

In all three trials, similar response rates were observed with pamidronate disodium treatment regardless of the presence or absence of bone metastases. Concomitant administration of furosemide did not affect response rates.

Thirty-two patients who had recurrent or refractory hypercalcemia of malignancy were given a second course of 60 mg of pamidronate disodium over a 4-or 24-hour period. Of these, 41% showed a complete response and 16% showed a partial response to the retreatment, and these responders had about a 3 mg/dL fall in mean-corrected serum calcium levels 7 days after retreatment.

In a fourth multicenter, randomized, double-blind trial, 103 patients with cancer and hypercalcemia (corrected serum calcium ≥ 12 mg/dL) received 90 mg of pamidronate disodium as a 2-hour infusion. The mean baseline corrected serum calcium was 14 mg/dL.

Patients were not required to receive IV hydration prior to drug administration, but all subjects did receive at least 500 mL of IV saline hydration concomitantly with the pamidronate infusion. By day 10 after drug infusion, 70% of patients had normal corrected serum calcium levels (< 10.8 mg/dL).

14.2 Paget’s Disease

In a double-blind clinical trial, 64 patients with moderate to severe Paget’s disease of bone received 5 mg, 15 mg, or 30 mg of pamidronate disodium as a single 4-hour infusion daily on 3 consecutive days, for total doses of 15 mg, 45 mg, and 90 mg of pamidronate disodium.

For the 15 mg, 45 mg, and 90 mg groups, mean baseline serum alkaline phosphatase levels were 1409 U/L, 983 U/L, and 1085 U/L, and mean baseline urine hydroxyproline/creatinine ratios were 0.25, 0.19, and 0.19, respectively.

The effects of pamidronate disodium on serum alkaline phosphatase (SAP) and urine hydroxyproline/creatinine ratios (UOHP/C) are summarized in Table 7.

Table 7: Percent of Patients with Decrease in SAP and UOHP/C
SAP |  |  |  | UOHP/C
% Decrease | 15 mg | 45 mg | 90 mg | 15 mg | 45 mg | 90 mg
≥ 50 | 26% | 33% | 60% | 15% | 47% | 72%
≥ 30 | 40% | 65% | 83% | 35% | 57% | 85%

For the 15 mg, 45 mg, and 90 mg groups, median maximum percent decreases from baseline in serum alkaline phosphatase were 25%, 41%, and 57%, and urine hydroxyproline/creatinine ratios were 25%, 47%, and 61%, respectively. The median time to response (≥ 50% decrease) for serum alkaline phosphatase was approximately 1 month for the 90 mg group, and the response duration ranged from 1 to 372 days.

Twenty-five patients who had Paget’s disease were retreated with 90 mg of pamidronate disodium. Of these, 44% had a ≥ 50% decrease in serum alkaline phosphatase from baseline after treatment, and 39% had a ≥ 50% decrease in urine hydroxyproline/creatinine ratio from baseline after treatment.

14.3 Osteolytic Bone Metastases of Breast Cancer and Osteolytic Lesions of Multiple Myeloma

Breast Cancer

Two double-blind, randomized, placebo-controlled trials compared the safety and efficacy of pamidronate disodium 90 mg infused over 2 hours every 3 to 4 weeks for 24 months to placebo for prevention of SREs in breast cancer patients with osteolytic bone metastases who had one or more predominantly lytic metastases of at least 1 cm in diameter. The first trial enrolled 382 patients receiving chemotherapy, of whom 185 were randomized to pamidronate disodium and 197 to placebo. The second trial enrolled 372 patients receiving hormonal therapy, of whom 182 were randomized to pamidronate disodium and 190 to placebo. All but three patients were evaluable for efficacy. Bone lesion response was radiographically assessed at baseline and at 3, 6, and 12 months. Therapy continued for 24 months unless patient discontinued study.

Median duration of follow-up was 13 months in patients receiving chemotherapy and 17 months in patients receiving hormone therapy. Twenty-five percent of the patients in the chemotherapy study and 37% of the patients in the hormone therapy study received pamidronate disodium for 24 months. Efficacy results are shown in Table 8:

Table 8: Efficacy Results in Breast Cancer Patients
N | Breast Cancer Patients Receiving Chemotherapy
N | Any SRE |  | Radiation |  | Fractures
N | Pamidronate disodium | Placebo | Pamidronate disodium | Placebo | Pamidronate disodium | Placebo
N | 185 | 195 | 185 | 195 | 185 | 195
Skeletal Morbidity Rate (#SRE/year) Mean | 2.5 | 3.7 | 0.8 | 1.3 | 1.6 | 2.2
P-Value | < .001 |  | < .001 [Fractures and radiation to bone were two of several secondary endpoints. The statistical significance of these analyses may be overestimated since numerous analyses were performed.] |  | .018
Proportion of patients having an SRE | 46% | 65% | 28% | 45% | 36% | 49%
P-Value | < .001 |  | < .001 |  | .014
Median Time to SRE (months) | 13.9 | 7.0 | NR [NR = Not Reached] | 14.2 | 25.8 | 13.3
P-Value | < .001 |  | < .001 |  | .009
N | Breast Cancer Patients Receiving Hormonal Therapy
N | Any SRE |  | Radiation |  | Fractures
N | Pamidronate disodium | Placebo | Pamidronate disodium | Placebo | Pamidronate disodium | Placebo
N | 182 | 189 | 182 | 189 | 182 | 189
Skeletal Morbidity Rate (#SRE/year) Mean | 2.4 | 3.6 | 0.6 | 1.2 | 1.6 | 2.2
P-Value | .021 |  | .013 |  | .040
Proportion of patients having an SRE | 55% | 63% | 31% | 40% | 45% | 55%
P-Value | .094 |  | .058 |  | .054
Median Time to SRE (months) | 10.9 | 7.4 | NR | 23.4 | 20.6 | 12.8
P-Value | .118 |  | .016 |  | .113

Advanced Multiple Myeloma

In a double-blind, randomized, placebo-controlled trial, 392 patients on therapy for advanced multiple myeloma received pamidronate disodium or placebo to determine the effect on the occurrence of skeletal-related events (SREs). SREs were defined as the occurrence of new or additional pathologic fractures, radiation therapy or surgery for bony fracture, impending fracture, or spinal cord compression. Pamidronate disodium 90 mg or placebo was administered as a 4-hour infusion every 4 weeks for 9 months. Of the 392 patients enrolled, 377 were evaluable for efficacy. Results are shown in Table 9.

Table 9: SRE Outcomes in Multiple Myeloma
 | Pamidronate disodium; 90 mg /4 hours (N = 196) | Placebo (N = 181) | P-value
At 1 year; % of Patients with SRE | 24% | 41% | P < 0.001
% with Pathological Fracture | 17% | 30% | P < 0.004
% with Radiation to Bone | 14% | 21% | P < 0.049
At 1.75 years (21 Months) % Pathologic Vertebral Fractures | 16% | 27% | P = 0.005

The times to the first SRE occurrence, pathologic fracture, and radiation to bone were significantly longer in the pamidronate disodium group (P = 0.001, 0.006, and 0.046, respectively). After 21 months, the proportion of patients experiencing any skeletal event remained significantly less in the pamidronate disodium group compared to the placebo group (P = 0.015). Time to first SRE was significantly longer in the pamidronate disodium group compared to placebo (P = 0.016). Survival was not different between treatment groups.

16 HOW SUPPLIED/STORAGE AND HANDLING

Pamidronate Disodium Injection is available as follows:

30 mg/10 mL (3 mg/mL) single-dose vial as a clear-colorless solution containing 30 mg of pamidronate disodium and 470 mg of mannitol in 10 mL water for injection.

NDC 67457-430-10
Carton of 1 single-dose vial

90 mg/10 mL (9 mg/mL) single-dose vial as a clear-colorless solution containing 90 mg of pamidronate disodium and 375 mg of mannitol in 10 mL water for injection.

NDC 67457-446-10
Carton of 1 single-dose vial

Storage: Store at 20°C to 25°C (68°F to 77°F) [See USP Controlled Room Temperature].

17 PATIENT COUNSELING INFORMATION

- Advise pregnant women and females of reproductive potential of the potential risk to a fetus and to inform their healthcare provider of a known or suspected pregnancy [see Warnings and Precautions (5.2), Use in Specific Populations (8.1)]. Advise females of reproductive potential to use effective contraception during and after pamidronate disodium treatment [see Use in Specific Populations (8.3)].
- Advise women not to breastfeed during and after pamidronate disodium treatment [see Use in Specific Populations (8.2)].
- Advise males and females of reproductive potential that pamidronate may impair fertility [see Use in Specific Populations (8.3)].
- Inform patients that the risk of osteonecrosis of the jaw is increased in patients undergoing invasive dental procedures. Advise patients to avoid such procedures, if possible, and to maintain good dental hygiene and routine dental care [see Warnings and Precautions (5.4)].
- Inform patients that atypical femur fractures have occurred in patients taking bisphosphonates. Advise patients to report any thigh or groin pain [see Warnings and Precautions (5.5)].

Manufactured for:
Mylan Institutional LLC
Morgantown, WV 26505 U.S.A.

Manufactured by:
OneSource Specialty Pharma Limited
(Sterile Product Division)
Bengaluru 560076, India

50107390
1200013667

Revised: 12/2025

PRINCIPAL DISPLAY PANEL – 3 mg/mL

NDC 67457-430-10

Pamidronate
Disodium
Injection

30 mg/10 mL
(3 mg/mL)

Sterile

Do not mix with
calcium containing
infusion solution

FURTHER DILUTION
REQUIRED

For Intravenous Infusion

Mylan

Rx only

Single-Dose Vial

Each vial contains:
Active: Pamidronate
Disodium 30 mg

Inactives: Mannitol
470 mg; Phosphoric acid
to adjust pH (6.0 to 7.0);
and Water for Injection q.s
to 10 mL.

Storage: Store at 20°
to 25°C (68° to 77°F).
[See USP Controlled
Room Temperature.]

Usual Dosage: See
Package Insert.

Important: Dilution and
administration differs
for each indication.

Discard unused portion.

Manufactured for:
Mylan Institutional LLC
Morgantown, WV 26505 U.S.A.

Made in India

Code No.:

KR/DRUGS/KTK/28/280/1995

Mylan.com

PRINCIPAL DISPLAY PANEL – 9 mg/mL

NDC 67457-446-10

Pamidronate
Disodium
Injection

90 mg/10 mL
(9 mg/mL)

Sterile

Do not mix with
calcium containing
infusion solution

FURTHER DILUTION
REQUIRED

For Intravenous Infusion

Mylan

Rx only

Single-Dose Vial

Each vial contains:
Active: Pamidronate
Disodium 90 mg

Inactives: Mannitol
375 mg; Phosphoric acid
to adjust pH (6.0 to 7.0);
and Water for Injection q.s
to 10 mL.

Storage: Store at 20°
to 25°C (68° to 77°F).
[See USP Controlled
Room Temperature.]

Usual Dosage: See
Package Insert.

Important: Dilution and
administration differs
for each indication.

Discard unused portion.

Manufactured for:
Mylan Institutional LLC
Morgantown, WV 26505 U.S.A.

Made in India

Code No.:

KR/DRUGS/KTK/28/280/1995

Mylan.com